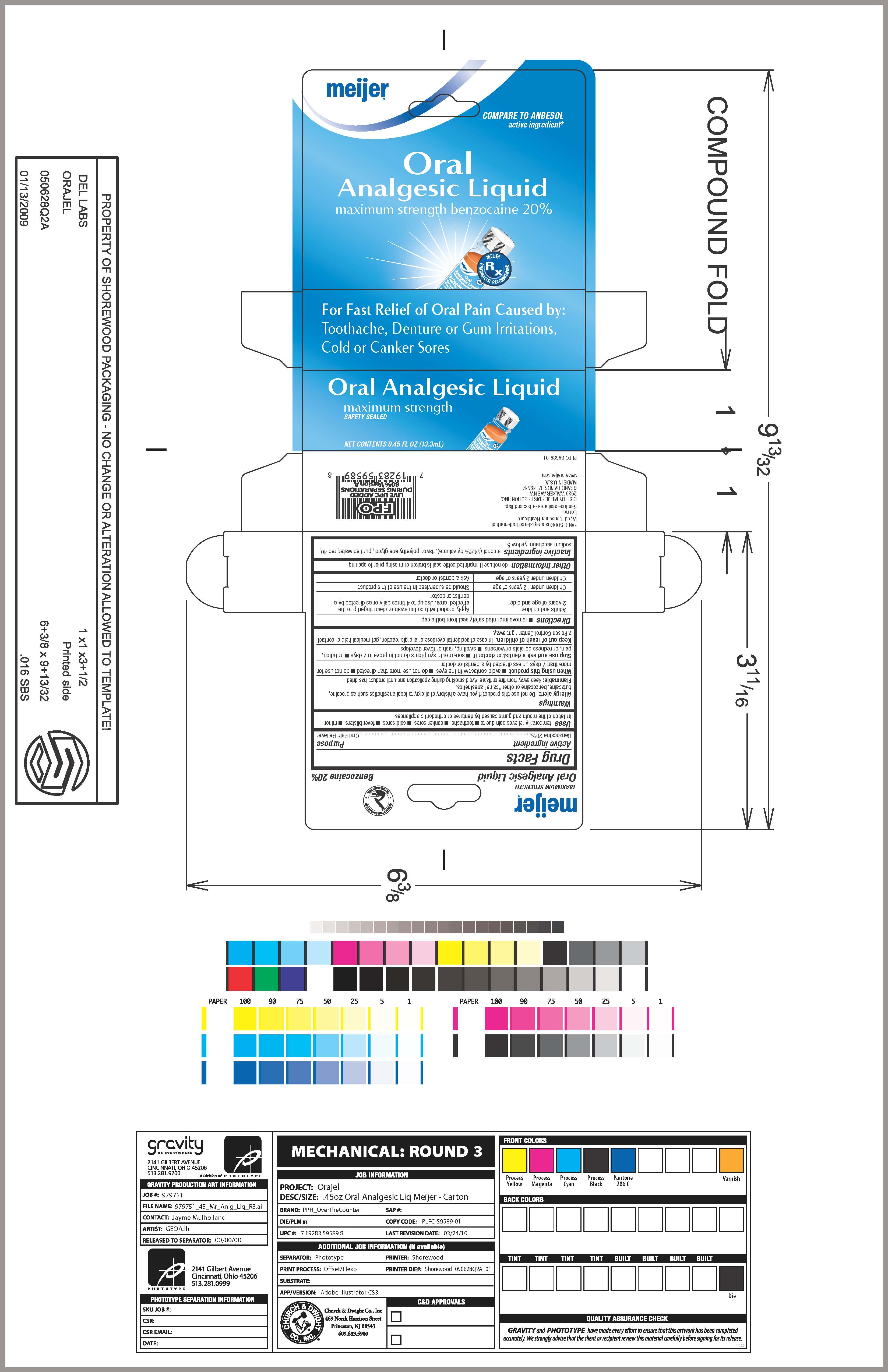 DRUG LABEL: Oral Analgesic 
NDC: 41250-703 | Form: LIQUID
Manufacturer: Meijer Distribution Inc.
Category: otc | Type: HUMAN OTC DRUG LABEL
Date: 20100513

ACTIVE INGREDIENTS: Benzocaine 0.2 mL/1 mL
INACTIVE INGREDIENTS: ALCOHOL; POLYETHYLENE GLYCOL 400; SACCHARIN SODIUM; WATER; FD&C RED NO. 40; FD&C YELLOW NO. 5

Drug Facts

Uses

Uses temporarily relieves pain due to toothache, canker sores, cold sores, fever blisters, minor irritation of the mouth and gums caused by dentures or orthodontic appliances

Warnings

Allergy alert: do not use this product if you have a history of allergy to local anesthetics such as procaine, butacaine, benzocaine or other "caine" anesthetics.

Flammable: keep away from fire or flame. Avoid smoking during applications and until product has dried.

When using this product avoid contact with the eyes, do not use more than directed, for more than 7 days unless directed by a dentist or doctor

Stop use and ask a doctor if sore mouth symptoms do not improve in 7 days; irritation, pain or redness persists or worsens; swelling, rash or fever develops;

Keep out of reach of children:

in case of overdose, get medical help or contact a Poison Control Center right away

Directions

Directions remove imprinted safety seal from bottle cap

Adults and children 2 years of age and over Apply product with cotton swab or clean fingertip to the affected area.
Use up to 4 times daily or as directed by a dentist or doctor

Children under 12 years of age Should be supervised in the use of this product
Children under 2 years of age Ask a dentist or doctor
Other information do not use if imprinted bottle seal is broken or missing prior to opening

Inactive ingredients

Inactive ingredients ammonium glycyrrhizate, flavor, polyethylene glycol, sodium saccharin, sorbic acid

Questions or comments? call us at 1-800-952-5080 M-F 9am-5pm ET

PACKAGE LABEL

Meijer
Oral Analgesic Liquid
maximum strength benzocaine 20%
For Fast Relief of Oral Pain Caused by:
Toothache, Denture or Gum Irritations,
Cold or Canker Sores
Oral Analgesic Liquid
maximum Strength
safety sealed tube tip
NET WT. 0.45 OZ (13.3g)
Carton Image